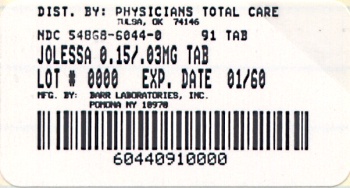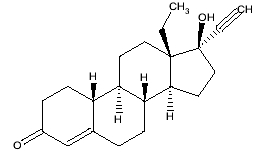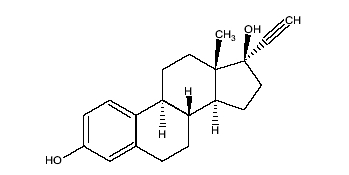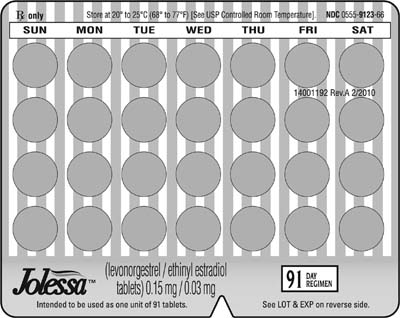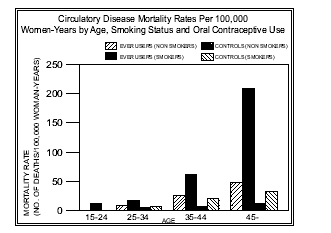 DRUG LABEL: Jolessa
NDC: 54868-6044 | Form: KIT | Route: ORAL
Manufacturer: Physicians Total Care, Inc.
Category: prescription | Type: HUMAN PRESCRIPTION DRUG LABEL
Date: 20110128

ACTIVE INGREDIENTS: LEVONORGESTREL 0.15 mg/1 1; ETHINYL ESTRADIOL 0.03 mg/1 1
INACTIVE INGREDIENTS: ANHYDROUS LACTOSE; FD&C BLUE NO. 1; FD&C RED NO. 40; HYPROMELLOSE 2208 (15000 MPA.S); MAGNESIUM STEARATE; CELLULOSE, MICROCRYSTALLINE; POLYETHYLENE GLYCOL; POLYSORBATE 80; TITANIUM DIOXIDE; ANHYDROUS LACTOSE; HYPROMELLOSE 2208 (15000 MPA.S); MAGNESIUM STEARATE; CELLULOSE, MICROCRYSTALLINE

Rx only

11001623
Revised February 2010

Jolessa™ (levonorgestrel / ethinyl estradiol tablets) 0.15 mg / 0.03 mg

Patients should be counseled that this product does not protect against HIV-infection (AIDS) and other sexually transmitted diseases.

BOXED WARNING

Cigarette smoking increases the risk of serious cardiovascular side effects from oral contraceptive use. This risk increases with age and with heavy smoking (15 or more cigarettes per day) and is quite marked in women over 35 years of age. Women who use oral contraceptives should be strongly advised not to smoke.

DESCRIPTION

Jolessa™ (levonorgestrel/ethinyl estradiol tablets) is an extended-cycle oral contraceptive consisting of 84 pink active tablets each containing 0.15 mg of levonorgestrel, a synthetic progestogen and 0.03 mg of ethinyl estradiol, and 7 white inert tablets (without hormones).

The chemical formula of levonorgestrel USP is 18,19-Dinorpregn-4-en-20-yn-3-one, 13-ethyl-17-hydroxy-, (17α)-, (-)-, and the chemical formula of ethinyl estradiol USP is 19-Norpregna-1,3,5(10)-trien-20-yne-3,17-diol, (17α)-. The structural formulas are as follows:

Levonorgestrel C21H28O2 MW: 312.4

Ethinyl Estradiol C20H24O2 MW: 296.4

Each pink active tablet contains the following inactive ingredients: anhydrous lactose NF, FD&C blue no. 1, FD&C red no. 40, hydroxypropyl methylcellulose USP, microcrystalline cellulose NF, polyethylene glycol NF, magnesium stearate NF, polysorbate 80 NF, and titanium dioxide USP. Each white inert tablet contains the following inactive ingredients: anhydrous lactose NF, hydroxypropyl methylcellulose USP, microcrystalline cellulose NF, and magnesium stearate NF.

CLINICAL PHARMACOLOGY

Mode of action

Combination oral contraceptives act by suppression of gonadotropins. Although the primary mechanism of this action is inhibition of ovulation, other alterations include changes in the cervical mucus (which increase the difficulty of sperm entry into the uterus) and changes in the endometrium (which reduce the likelihood of implantation).

Pharmacokinetics Absorption

No specific investigation of the absolute bioavailability of Jolessa™ in humans has been conducted. However, literature indicates that levonorgestrel is rapidly and completely absorbed after oral administration (bioavailability nearly 100%) and is not subject to first-pass metabolism. Ethinyl estradiol is rapidly and almost completely absorbed from the gastrointestinal tract but, due to first-pass metabolism in gut mucosa and liver, the bioavailability of ethinyl estradiol is approximately 43%.

Table 1: Mean ± SD Pharmacokinetic Parameters Following A Single Dose Administration of Two Tablets of Jolessa™ in Healthy Female Subjects Under Fasting Conditions
Analyte | AUCt (mean ± SD) | Cmax (mean ± SD) | Tmax (mean ± SD) | T1/2 (mean ± SD)
Levonorgestrel | 60.8 ± 25.6 ng*hr/mL | 5.6 ± 1.5 ng/mL | 1.4 ± 0.3 hours | 29.8 ± 8.3 hours
Ethinyl estradiol | 1307 ± 361 pg*hr/mL | 145 ± 45 pg/mL | 1.6 ± 0.5 hours | 15.4 ± 3.2 hours

The effect of food on the rate and the extent of levonorgestrel and ethinyl estradiol absorption following oral administration of Jolessa™ has not been evaluated.

Distribution

The apparent volume of distribution of levonorgestrel and ethinyl estradiol are reported to be approximately 1.8 L/kg and 4.3 L/kg, respectively. Levonorgestrel is about 97.5 - 99% protein-bound, principally to sex hormone binding globulin (SHBG) and, to a lesser extent, serum albumin. Ethinyl estradiol is about 95 - 97% bound to serum albumin. Ethinyl estradiol does not bind to SHBG, but induces SHBG synthesis, which leads to decreased levonorgestrel clearance. Following repeated daily dosing of combination levonorgestrel/ethinyl estradiol oral contraceptives, levonorgestrel plasma concentrations accumulate more than predicted based on single-dose kinetics, due in part, to increased SHBG levels that are induced by ethinyl estradiol, and a possible reduction in hepatic metabolic capacity.

Metabolism

Following absorption, levonorgestrel is conjugated at the 17β-OH position to form sulfate and to a lesser extent, glucuronide conjugates in plasma. Significant amounts of conjugated and unconjugated 3α,5β-tetrahydrolevonorgestrel are also present in plasma, along with much smaller amounts of 3α,5α-tetrahydrolevonorgestrel and 16β-hydroxylevonorgestrel. Levonorgestrel and its phase I metabolites are excreted primarily as glucuronide conjugates. Metabolic clearance rates may differ among individuals by several-fold, and this may account in part for the wide variation observed in levonorgestrel concentrations among users.

First-pass metabolism of ethinyl estradiol involves formation of ethinyl estradiol-3-sulfate in the gut wall, followed by 2-hydroxylation of a portion of the remaining untransformed ethinyl estradiol by hepatic cytochrome P-450 3A4 (CYP3A4). Levels of CYP3A4 vary widely among individuals and can explain the variation in rates of ethinyl estradiol hydroxylation. Hydroxylation at the 4-, 6-, and 16- positions may also occur, although to a much lesser extent than 2-hydroxylation. The various hydroxylated metabolites are subject to further methylation and/or conjugation.

Excretion

About 45% of levonorgestrel and its metabolites are excreted in the urine and about 32% are excreted in feces, mostly as glucuronide conjugates. The terminal elimination half-life for levonorgestrel after a single dose of Jolessa™ was about 30 hours.

Ethinyl estradiol is excreted in the urine and feces as glucuronide and sulfate conjugates, and it undergoes enterohepatic recirculation. The terminal elimination half-life of ethinyl estradiol after a single dose of Jolessa™ was found to be about 15 hours.

SPECIAL POPULATIONS

Race

No formal studies on the effect of race on the pharmacokinetics of Jolessa™ were conducted.

Hepatic Insufficiency

No formal studies have been conducted to evaluate the effect of hepatic disease on the pharmacokinetics of Jolessa™. However, steroid hormones may be poorly metabolized in patients with impaired liver function.

Renal Insufficiency

No formal studies have been conducted to evaluate the effect of renal disease on the pharmacokinetics of Jolessa™.

Drug-Drug Interactions

See PRECAUTIONS section – Drug Interactions.

INDICATIONS AND USAGE

Jolessa™ tablets are indicated for the prevention of pregnancy in women who elect to use oral contraceptives as a method of contraception.

In a 1-year controlled clinical trial, 4 pregnancies occurred in women 18-35 years of age during 809 completed 91-day cycles of Jolessa™ during which no backup contraception was utilized. This represents an overall use-efficacy (typical user efficacy) pregnancy rate of 1.98 per 100 women-years of use.

Oral contraceptives are highly effective for pregnancy prevention. Table 2 lists the typical unintended pregnancy rates for users of combination oral contraceptives and other methods of contraception. The efficacy of these contraceptive methods, except sterilization, the IUD, and Norplant® Implant System, depends upon the reliability with which they are used. Correct and consistent use of methods can result in lower failure rates.

TABLE 2 Percentage of women experiencing an unintended pregnancy during the first year of typical use and the first year of perfect use of contraception and the percentage continuing use at the end of the first year: United States.
 | % of Women Experiencing an Unintended Pregnancy within the First Year of Use | % of Women Continuing Use at One Year*
Method (1) | Typical Use† (2) | Perfect Use‡ (3) | (4)
Chance§ | 85 | 85
Spermicides¶ | 26 | 6 | 40
Periodic abstinence | 25 |  | 63
Calendar |  | 9
Ovulation method |  | 3
Sympto-thermal # |  | 2
Post-ovulation |  | 1
Withdrawal | 19 | 4
Cap Þ
Parous women | 40 | 26 | 42
Nulliparous women | 20 | 9 | 56
Sponge
Parous women | 40 | 20 | 42
Nulliparous women | 20 | 9 | 56
Diaphragm Þ | 20 | 6 | 56
Condom ß
Female (Reality) | 21 | 5 | 56
Male | 14 | 3 | 61
Pill | 5 |  | 71
Progestin only |  | 0.5
Combined |  | 0.1
IUD:
Progesterone T | 2.0 | 1.5 | 81
Copper T 380A | 0.8 | 0.6 | 78
LNg 20 | 0.1 | 0.1 | 81
Depo Provera | 0.3 | 0.3 | 70
Norplant and Norplant-2 | 0.05 | 0.05 | 88
Female sterilization | 0.5 | 0.5 | 100
Male sterilization | 0.15 | 0.10 | 100

Emergency Contraceptive Pills: Treatment initiated within 72 hours after unprotected intercourse reduces the risk of pregnancy by at least 75%. à
Lactational Amenorrhea Method: LAM is a highly effective, temporary method of contraception. è
Source: Trussell J, Contraceptive efficacy. In Hatcher RA, Trussell J, Stewart F, Cates W, Stewart GK, Kowal D, Guest F, Contraceptive Technology: Seventeenth Revised Edition. New York NY: Irvington Publishers, 1998.
*Among couples attempting to avoid pregnancy, the percentage who continue to use a method for one year.†Among typical couples who initiate use of a method (not necessarily for the first time), the percentage who experience an unintended pregnancy during the first year if they do not stop use for any other reason.‡Among couples who initiate use of a method (not necessarily for the first time) and who use it perfectly (both consistently and correctly), the percentage who experience an unintended pregnancy during the first year if they do not stop use for any other reason.§The percentages of women becoming pregnant in columns (2) and (3) are based on data from populations where contraception is not used and from women who cease using contraception in order to become pregnant. Among such populations, about 89% become pregnant within one year. This estimate was lowered slightly (to 85%) to represent the percentage who would become pregnant within one year among women now relying on reversible methods of contraception if they abandoned contraception altogether.¶Foams, creams, gels, vaginal suppositories and vaginal film.#Cervical mucus (ovulation) method supplemented by calendar in the pre-ovulatory and basal body temperature in the post-ovulatory phases.ÞWith spermicidal cream or jelly.ßWithout spermicides.àThe treatment schedule is one dose within 72 hours after unprotected intercourse and a second dose 12 hours after the first dose. The Food and Drug Administration has declared the following brands of oral contraceptives to be safe and effective for emergency contraception: Ovral (1 dose is 2 white pills), Alesse (1 dose is 5 pink pills), Nordette or Levlen (1 dose is 2 light-orange pills), Lo/Ovral (1 dose is 4 white pills), Triphasil or Tri-Levlen (1 dose is 4 yellow pills).èHowever, to maintain effective protection against pregnancy, another method of contraception must be used as soon as menstruation resumes, the frequency or duration of breastfeeds is reduced, bottle feeds are introduced or the baby reaches six months of age.

CONTRAINDICATIONS

Oral contraceptives should not be used in women who currently have the following conditions:

- Thrombophlebitis or thromboembolic disorders
- A past history of deep vein thrombophlebitis or thromboembolic disorders
- Cerebrovascular or coronary artery disease (current or history)
- Valvular heart disease with thrombogenic complications
- Uncontrolled hypertension
- Diabetes with vascular involvement
- Headaches with focal neurological symptoms
- Major surgery with prolonged immobilization
- Known or suspected carcinoma of the breast or personal history of breast cancer
- Carcinoma of the endometrium or other known or suspected estrogen-dependent neoplasia
- Undiagnosed abnormal genital bleeding
- Cholestatic jaundice of pregnancy or jaundice with prior pill use
- Hepatic adenomas or carcinomas, or active liver disease
- Known or suspected pregnancy
- Hypersensitivity to any component of this product

WARNINGS

Cigarette smoking increases the risk of serious cardiovascular side effects from oral contraceptive use. This risk increases with age and with heavy smoking (15 or more cigarettes per day) and is quite marked in women over 35 years of age. Women who use oral contraceptives should be strongly advised not to smoke.

The use of oral contraceptives is associated with increased risk of several serious conditions including venous and arterial thrombotic and thromboembolic events (such as myocardial infarction, thromboembolism, and stroke), hepatic neoplasia, gallbladder disease, and hypertension. The risk of serious morbidity or mortality is very small in healthy women without underlying risk factors. The risk of morbidity and mortality increases significantly in the presence of other underlying risk factors such as certain inherited thrombophilias, hypertension, hyperlipidemias, obesity and diabetes.

Practitioners prescribing oral contraceptives should be familiar with the following information relating to these risks. The information contained in this package insert is principally based on studies carried out in patients who used oral contraceptives with higher formulations of estrogens and progestogens than those in common use today. The effect of longterm use of the oral contraceptives with lower doses of both estrogens and progestogens remains to be determined.

Throughout this labeling, epidemiological studies reported are of two types: retrospective or case control studies and prospective or cohort studies. Case control studies provide a measure of the relative risk of a disease, namely, a ratio of the incidence of a disease among oral contraceptive users to that among nonusers. The relative risk does not provide information on the actual clinical occurrence of a disease. Cohort studies provide a measure of attributable risk, which is the difference in the incidence of disease between oral contraceptive users and nonusers. The attributable risk does provide information about the actual occurrence of a disease in the population. For further information, the reader is referred to a text on epidemiological methods.

1. Thromboembolic Disorders and Other Vascular Problems

Use of Jolessa™ provides women with more hormonal exposure on a yearly basis than conventional monthly oral contraceptives containing similar strength synthetic estrogens and progestins (an additional 9 weeks per year). While this added exposure may pose an additional risk of thrombotic and thromboembolic disease, studies to date with Jolessa™ have not suggested an increased risk of these disorders.

a. Myocardial Infarction:

An increased risk of myocardial infarction has been attributed to oral contraceptive use. This risk is primarily in smokers or women with other underlying risk factors for coronary artery disease such as hypertension, hypercholesterolemia, morbid obesity, and diabetes. The relative risk of heart attack for current oral contraceptive users has been estimated to be two to six. The risk is very low under the age of 30. Smoking in combination with oral contraceptive use has been shown to contribute substantially to the incidence of myocardial infarction in women in their mid-thirties or older with smoking accounting for the majority of excess cases. Mortality rates associated with circulatory disease have been shown to increase substantially in smokers over the age of 35 and nonsmokers over the age of 40 (Figure 1) among women who use oral contraceptives.

Figure 1 Adapted from P.M. Layde and B Beral, Lancet, 1 :541-546,1981

Oral contraceptives may compound the effects of well-known risk factors, such as hypertension, diabetes, hyperlipidemias, age and obesity. In particular, some progestogens are known to decrease HDL cholesterol and cause glucose intolerance, while estrogens may create a state of hyperinsulinism. Oral contraceptives have been shown to increase blood pressure among users (see section 9 in WARNINGS). The severity and number of risk factors increase heart disease risk. Oral contraceptives must be used with caution in women with cardiovascular disease risk factors.

b. Thromboembolism:

An increased risk of thromboembolic and thrombotic disease associated with the use of oral contraceptives is well established. Case control studies have found the relative risk of users compared to nonusers to be 3 for the first episode of superficial venous thrombosis, 4 to 11 for deep vein thrombosis or pulmonary embolism, and 1.5 to 6 for women with predisposing conditions for venous thromboembolic disease. Cohort studies have shown the relative risk to be somewhat lower, about 3 for new cases and about 4.5 for new cases requiring hospitalization. The approximate incidence of deep vein thrombosis and pulmonary embolism in users of low dose (<50 μg ethinyl estradiol) combination oral contraceptives is up to 4 per 10,000 woman-years compared to 0.5-3 per 10,000 woman-years for non-users. However, the incidence is less than that associated with pregnancy (6 per 10,000 woman-years). The risk of thromboembolic disease due to oral contraceptives is not related to length of use and disappears after pill use is stopped.

A two- to four-fold increase in relative risk of postoperative thromboembolic complications has been reported with the use of oral contraceptives. The relative risk of venous thrombosis in women who have predisposing conditions is twice that of women without such medical conditions. If feasible, oral contraceptives should be discontinued at least four weeks prior to and for two weeks after elective surgery of a type associated with an increase in risk of thromboembolism and during and following prolonged immobilization. Since the immediate postpartum period is also associated with an increased risk of thromboembolism, oral contraceptives should be started no earlier than four weeks after delivery in women who elect not to breast-feed.

c. Cerebrovascular Diseases:

Oral contraceptives have been shown to increase both the relative and attributable risks of cerebrovascular events (thrombotic and hemorrhagic strokes), although, in general, the risk is greatest among older (>35 years), hypertensive women who also smoke. Hypertension was found to be a risk factor for both users and nonusers, for both types of strokes, while smoking interacted to increase the risk for hemorrhagic strokes.

In a large study, the relative risk of thrombotic strokes has been shown to range from 3 for normotensive users to 14 for users with severe hypertension. The relative risk of hemorrhagic stroke is reported to be 1.2 for nonsmokers who used oral contraceptives, 2.6 for smokers who did not use oral contraceptives, 7.6 for smokers who used oral contraceptives, 1.8 for normotensive users and 25.7 for users with severe hypertension. The attributable risk is also greater in older women. Oral contraceptives also increase the risk for stroke in women with other underlying risk factors such as certain inherited or acquired thrombophilias, hyperlipidemias, and obesity. Women with migraine (particularly migraine with aura) who take combination oral contraceptives may be at an increased risk of stroke.

d. Dose-Related Risk of Vascular Disease from Oral Contraceptives:

A positive association has been observed between the amount of estrogen and progestogen in oral contraceptives and the risk of vascular disease. A decline in serum high-density lipoproteins (HDL) has been reported with many progestational agents. A decline in serum high-density lipoproteins has been associated with an increased incidence of ischemic heart disease.

Because estrogens increase HDL cholesterol, the net effect of an oral contraceptive depends on a balance achieved between doses of estrogen and progestogen and the nature and absolute amount of progestogen used in the contraceptive. The amount of both hormones should be considered in the choice of an oral contraceptive.

Minimizing exposure to estrogen and progestogen is in keeping with good principles of therapeutics. For any particular estrogen/progestogen combination, the dosage regimen prescribed should be one which contains the least amount of estrogen and progestogen that is compatible with a low failure rate and the needs of the individual patient. New acceptors of oral contraceptive agents should be started on preparations containing the lowest estrogen content which is judged appropriate for the individual patient.

e. Persistence of Risk of Vascular Disease:

There are two studies which have shown persistence of risk of vascular disease for ever-users of oral contraceptives. In a study in the United States, the risk of developing myocardial infarction after discontinuing oral contraceptives persists for at least 9 years for women 40 to 49 years old who had used oral contraceptives for five or more years, but this increased risk was not demonstrated in other age groups. In another study in Great Britain, the risk of developing cerebrovascular disease persisted for at least 6 years after discontinuation of oral contraceptives, although excess risk was very small. However, both studies were performed with oral contraceptive formulations containing 50 micrograms or higher of estrogens.

2. Estimates of Mortality from Contraceptive Use

One study gathered data from a variety of sources which have estimated the mortality rate associated with different methods of contraception at different ages (Table 3). These estimates include the combined risk of death associated with contraceptive methods plus the risk attributable to pregnancy in the event of method failure. Each method of contraception has its specific benefits and risks. The study concluded that with the exception of oral contraceptive users 35 and older who smoke and 40 and older who do not smoke, mortality associated with all methods of birth control is less than that associated with childbirth. The observation of a possible increase in risk of mortality with age for oral contraceptive users is based on data gathered in the 1970’s—but not reported until 1983. However, current clinical practice involves the use of lower estrogen dose formulations combined with careful restriction of oral contraceptive use to women who do not have the various risk factors listed in this labeling.

Because of these changes in practice and, also, because of some limited new data which suggest that the risk of cardiovascular disease with the use of oral contraceptives may now be less than previously observed, the Fertility and Maternal Health Drugs Advisory Committee was asked to review the topic in 1989. The Committee concluded that although cardiovascular disease risks may be increased with oral contraceptive use after age 40 in healthy nonsmoking women (even with the newer low-dose formulations), there are greater potential health risks associated with pregnancy in older women and with the alternative surgical and medical procedures which may be necessary if such women do not have access to effective and acceptable means of contraception.

Therefore, the Committee recommended that the benefits of oral contraceptive use by healthy nonsmoking women over 40 may outweigh the possible risks. Of course, older women, as all women who take oral contraceptives, should take the lowest possible dose formulation that is effective.

that is effective.

TABLE 3: ANNUAL NUMBER OF BIRTH-RELATED OR METHOD-RELATED DEATHS ASSOCIATED WITH CONTROL OF FERTILITY PER 100,000 NONSTERILE WOMEN, BY FERTILITY-CONTROL METHOD AND ACCORDING TO AGE
Method of control and outcome | 15-19 | 20-24 | AGE 25-29 | 30-34 | 35-39 | 40-44
No fertility - control methods* | 7.0 | 7.4 | 9.1 | 14.8 | 25.7 | 28.2
Oral contraceptives non-smoker† | 0.3 | 0.5 | 0.9 | 1.9 | 13.8 | 31.6
Oral contraceptives smoker† | 2.2 | 3.4 | 6.6 | 13.5 | 51.1 | 117.2
IUD† | 0.8 | 0.8 | 1.0 | 1.0 | 1.4 | 1.4
Condom* | 1.1 | 1.6 | 0.7 | 0.2 | 0.3 | 0.4
Diaphragm/ spermicide* | 1.9 | 1.2 | 1.2 | 1.3 | 2.2 | 2.8
Periodic abstinence* | 2.5 | 1.6 | 1.6 | 1.7 | 2.9 | 3.6

Adapted from H.W. Ory, Family Planning Perpectives, 15:57-63, 1983.
*Deaths are birth related†Deaths are method related
3. Carcinoma of the Reproductive Organs and Breasts

Numerous epidemiological studies have been performed on the incidence of breast, endometrial, ovarian and cervical cancer in women using oral contraceptives. Although the risk of having breast cancer diagnosed may be slightly increased among current and recent users of combined oral contraceptives (RR=1.24), this excess risk decreases over time after combination oral contraceptive discontinuation and by 10 years after cessation the increased risk disappears. The risk does not increase with duration of use and no consistent relationships have been found with dose or type of steroid. The patterns of risk are also similar regardless of a woman’s reproductive history or her family breast cancer history. The subgroup for whom risk has been found to be significantly elevated is women who first used oral contraceptives before age 20, but because breast cancer is so rare at these young ages, the number of cases attributable to this early oral contraceptive use is extremely small. Breast cancers diagnosed in current or previous oral contraceptive users tend to be less clinically advanced than in never-users. Women who currently have or have had breast cancer should not use oral contraceptives because breast cancer is a hormone sensitive tumor.

Some studies suggest that oral contraceptive use has been associated with an increase in the risk of cervical intraepithelial neoplasia or invasive cervical cancer in some populations of women. However, there continues to be controversy about the extent to which such findings may be due to differences in sexual behavior and other factors. In spite of many studies of the relationship between oral contraceptive use and breast cancer and cervical cancers, a cause and-effect relationship has not been established.

4. Hepatic Neoplasia

Benign hepatic adenomas are associated with oral contraceptive use, although their occurrence is rare in the United States. Indirect calculations have estimated the attributable risk to be in the range of 3.3 cases/100,000 for users, a risk that increases after four or more years of use. Rupture of hepatic adenomas may cause death through intra-abdominal hemorrhage.

Studies from Britain have shown an increased risk of developing hepatocellular carcinoma in long-term (>8 years) oral contraceptive users. However, these cancers are extremely rare in the U.S., and the attributable risk (the excess incidence) of liver cancers in oral contraceptive users approaches less than one per million users.

5. Ocular Lesions

There have been clinical case reports of retinal thrombosis associated with the use of oral contraceptives that may lead to partial or complete loss of vision. Oral contraceptives should be discontinued if there is unexplained partial or complete loss of vision; onset of proptosis or diplopia; papilledema; or retinal vascular lesions. Appropriate diagnostic and therapeutic measures should be undertaken immediately.

6. Oral contraceptive Use Before or During Early Pregnancy

Because women using Jolessa™ will likely have withdrawal bleeding only 4 times per year, pregnancy should be ruled out at the time of any missed menstrual period (see DOSAGE AND ADMINISTRATION section). Oral contraceptive use should be discontinued if pregnancy is confirmed.

Extensive epidemiological studies have revealed no increased risk of birth defects in women who have used oral contraceptives prior to pregnancy. Studies also do not suggest a teratogenic effect, particularly in so far as cardiac anomalies and limb-reduction defects are concerned, when taken inadvertently during early pregnancy (see CONTRAINDICATIONS section).

The administration of oral contraceptives to induce withdrawal bleeding should not be used as a test for pregnancy. Oral contraceptives should not be used during pregnancy to treat threatened or habitual abortion.

7. Gallbladder Disease

Earlier studies have reported an increased lifetime relative risk of gallbladder surgery in users of oral contraceptives and estrogens. More recent studies, however, have shown that the relative risk of developing gallbladder disease among oral contraceptive users may be minimal. The recent findings of minimal risk may be related to the use of oral contraceptive formulations containing lower hormonal doses of estrogens and progestogens.

8. Carbohydrate and Lipid Metabolic Effects

Oral contraceptives have been shown to cause glucose intolerance in a significant percentage of users. Oral contraceptives containing greater than 75 micrograms of estrogens cause hyperinsulinism, while lower doses of estrogen cause less glucose intolerance. Progestogens increase insulin secretion and create insulin resistance, this effect varying with different progestational agents. However, in the nondiabetic woman, oral contraceptives appear to have no effect on fasting blood glucose. Because of these demonstrated effects, prediabetic and diabetic women should be carefully observed while taking oral contraceptives.

A small proportion of women will have persistent hypertriglyceridemia while on the pill. As discussed earlier (see WARNINGS 1a. and 1d.), changes in serum triglycerides and lipoprotein levels have been reported in oral contraceptive users.

9. Elevated Blood Pressure

Women with significant hypertension should not be started on hormonal contraceptive. An increase in blood pressure has been reported in women taking oral contraceptives and this increase is more likely in older oral contraceptive users and with continued use. Data from the Royal College of General Practitioners and subsequent randomized trials have shown that the incidence of hypertension increases with increasing concentrations of progestogens.

Women with a history of hypertension or hypertension-related diseases, or renal disease should be encouraged to use another method of contraception. If women with hypertension elect to use oral contraceptives, they should be monitored closely, and if significant elevation of blood pressure occurs, oral contraceptives should be discontinued (see CONTRAINDICATIONS section). For most women, elevated blood pressure will return to normal after stopping oral contraceptives, and there is no difference in the occurrence of hypertension among ever- and never-users.

10. Headache

The onset or exacerbation of migraine or development of headache with a new pattern that is recurrent, persistent, or severe requires discontinuation of oral contraceptives and evaluation of the cause. (See WARNINGS, 1c.)

11. Bleeding Irregularities

When prescribing Jolessa™, the convenience of fewer planned menses (4 per year instead of 13 per year) should be weighed against the inconvenience of increased intermenstrual bleeding and/or spotting.

The clinical trial (SEA 301) that compared the efficacy of Jolessa™ (91-day cycles) to an equivalent dosage 28-day cycle regimen also assessed intermenstrual bleeding. The participants in the study were composed primarily of women who had used oral contraceptives previously as opposed to new users. Women with a history of breakthrough bleeding/spotting ≥10 consecutive days on oral contraceptives were excluded from the study. More Jolessa™ subjects, compared to subjects on the 28-day cycle regimen, discontinued prematurely for unacceptable bleeding (7.7% [Jolessa™] vs. 1.8% [28-day cycle regimen]).

Table 4 shows the percentages of women with ≥ 7 days and ≥ 20 days of intermenstrual spotting and/or bleeding in the Jolessa™ and the 28-day cycle treatment groups.

Table 4. Percentage of Subjects with Intermenstrual Bleeding and/or Spotting
Days of intermenstrual bleeding and/or spotting | Percentage of Subjects*
Jolessa™ | Cycle 1 (N=385) | Cycle 4 (N=261)
≥ 7 days | 65% | 42%
≥ 20 days | 35% | 15%
28-day regimen | Cycles 1-4 (N=194) | Cycles 10-13 (N=158)
≥ 7 days | 38% | 39%
≥ 20 days | 6% | 4%

*Based on spotting and/or bleeding on days 1-84 of a 91 day cycle in the Jolessa™ subjects and days 1-21 of a 28 day cycle over 4 cycles in the 28-day dosing regimen

Total days of bleeding and/or spotting (withdrawal plus intermenstrual) were similar over one year of treatment for Jolessa™ subjects and subjects on the 28-day cycle regimen.

As in any case of bleeding irregularities, nonhormonal causes should always be considered and adequate diagnostic measures taken to rule out malignancy or pregnancy.

In the event of amenorrhea, pregnancy should be ruled out. Some women may encounter post-pill amenorrhea or oligomenorrhea (possibly with anovulation), especially when such a condition was preexistent.

PRECAUTIONS

1. Sexually Transmitted Diseases

Patients should be counseled that this product does not protect against HIV infection (AIDS) and other sexually transmitted diseases.

2. Physical Examination and Follow-up

A periodic history and physical examination are appropriate for all women, including women using oral contraceptives. The physical examination, however, may be deferred until after initiation of oral contraceptives if requested by the woman and judged appropriate by the clinician. The physical examination should include special reference to blood pressure, breasts, abdomen and pelvic organs, including cervical cytology, and relevant laboratory tests. In the case of undiagnosed, persistent or recurrent abnormal vaginal bleeding, appropriate diagnostic measures should be conducted to rule out malignancy. Women with a strong family history of breast cancer or who have breast nodules should be monitored with particular care.

3. Lipid Disorders

Women who are being treated for hyperlipidemias should be followed closely if they elect to use oral contraceptives.

Some progestogens may elevate LDL levels and may render the control of hyperlipidemias more difficult. (See WARNINGS 1d.)

In patients with familial defects of lipoprotein metabolism receiving estrogen-containing preparations, there have been case reports of significant elevations of plasma triglycerides leading to pancreatitis.

4. Liver Function

If jaundice develops in any woman receiving such drugs, the medication should be discontinued. Steroid hormones may be poorly metabolized in patients with impaired liver function.

5. Fluid Retention

Oral contraceptives may cause some degree of fluid retention. They should be prescribed with caution, and only with careful monitoring, in patients with conditions which might be aggravated by fluid retention.

6. Emotional Disorders

Women with a history of depression should be carefully observed and the drug discontinued if depression recurs to a serious degree. Patients becoming significantly depressed while taking oral contraceptives should stop the medication and use an alternate method of contraception in an attempt to determine whether the symptom is drug related.

7. Contact Lenses

Contact-lens wearers who develop visual changes or changes in lens tolerance should be assessed by an ophthalmologist.

8. Drug Interactions

Changes in contraceptive effectiveness associated with co-administration of other products

a. Anti-infective agents and anticonvulsants

Contraceptive effectiveness may be reduced when hormonal contraceptives are co-administered with antibiotics, anticonvulsants, and other drugs that increase the metabolism of contraceptive steroids. This could result in unintended pregnancy or breakthrough bleeding. Examples include rifampin, barbiturates, phenylbutazone, phenytoin, carbamazepine, felbamate, oxcarbazepine, topiramate, and griseofulvin. Several cases of contraceptive failure and breakthrough bleeding have been reported in the literature with concomitant administration of antibiotics such as ampicillin and tetracyclines. However, clinical pharmacology studies investigating drug interaction between combined oral contraceptives and these antibiotics have reported inconsistent results.

b. Anti-HIV protease inhibitors

Several of the anti-HIV protease inhibitors have been studied with co-administration of combination oral contraceptives; significant changes (increase and decrease) in the plasma levels of the estrogen and progestin have been noted in some cases. The safety and efficacy of combination oral contraceptive products may be affected with co-administration of anti-HIV protease inhibitors. Healthcare providers should refer to the label of the individual anti-HIV protease inhibitors for further drug-drug interaction information.

c. Herbal products

Herbal products containing St. John’s Wort (hypericum perforatum) may induce hepatic enzymes (cytochrome P450) and p-glycoprotein transporter and may reduce the effectiveness of contraceptive steroids. This may also result in breakthrough bleeding.

Increase in plasma levels of estradiol associated with co-administered drugs

Co-administration of atorvastatin and certain combination oral contraceptives containing ethinyl estradiol increase AUC values for ethinyl estradiol by approximately 20%. Ascorbic acid and acetaminophen may increase plasma ethinyl estradiol levels, possibly by inhibition of conjugation. CYP 3A4 inhibitors such as itraconazole or ketoconazole may increase plasma hormone levels.

Changes in plasma levels of co-administered drugs

Combination oral contraceptives containing some synthetic estrogens (e.g., ethinyl estradiol) may inhibit the metabolism of other compounds. Increased plasma concentrations of cyclosporin, prednisolone, and theophylline have been reported with concomitant administration of combination oral contraceptives. Decreased plasma concentrations of acetaminophen and increased clearance of temazepam, salicylic acid, morphine and clofibric acid, due to induction of conjugation have been noted when these drugs were administered with combination oral contraceptives. Combination OCs have been shown to significantly decrease plasma concentrations of lamotrigine likely due to induction of lamotrigine glucuronidation. This may reduce seizure control; therefore, dosage adjustments of lamotrigine may be necessary. Consult the labeling of the concurrently-used drug to obtain further information about interactions with COCs or the potential for enzyme alterations.

9. Interactions with Laboratory Tests

Certain endocrine and liver function tests and blood components may be affected by oral contraceptives:

a. Increased prothrombin and factors VII, VIII, IX, and X; decreased antithrombin 3; increased norepinephrine-induced platelet aggregability. b. Increased thyroid-binding globulin (TBG) leading to increased circulating total thyroid hormone, as measured by protein-bound iodine (PBI), T4 by column or by radioimmunoassay. Free T3 resin uptake is decreased, reflecting the elevated TBG, free T4 concentration is unaltered. c. Other binding proteins may be elevated in serum. d. Sex hormone binding globulins are increased and result in elevated levels of total circulating sex steroids and corticoids; however, free or biologically active levels remain unchanged. e. Triglycerides may be increased and levels of various other lipids and lipoproteins may be affected. f. Glucose tolerance may be decreased. g. Serum folate levels may be depressed by oral contraceptive therapy. This may be of clinical significance if a woman becomes pregnant shortly after discontinuing oral contraceptives.10. Carcinogenesis

See WARNINGS section.

11. Pregnancy

Pregnancy Category X. See CONTRAINDICATIONS and WARNINGS sections.

12. Nursing Mothers

Small amounts of oral contraceptive steroids and/or metabolites have been identified in the milk of nursing mothers, and a few adverse effects on the child have been reported, including jaundice and breast enlargement. In addition, oral contraceptives given in the postpartum period may interfere with lactation by decreasing the quantity and quality of breast milk. If possible, the nursing mother should be advised not to use oral contraceptives but to use other forms of contraception until she has completely weaned her child.

13. Pediatric Use

Safety and efficacy of Jolessa™ tablets have been established in women of reproductive age. Safety and efficacy are expected to be the same in postpubertal adolescents under the age of 16 and users 16 and older. Use of Jolessa™ before menarche is not indicated.

14. Geriatric Use

Jolessa™ tablets have not been studied in women who have reached menopause.

INFORMATION FOR PATIENT

See Patient Labeling Printed Below.

ADVERSE REACTIONS

An increased risk of the following serious adverse reactions has been associated with the use of oral contraceptives (see WARNINGS section):

- Thrombophlebitis
- Arterial thromboembolism
- Pulmonary embolism
- Myocardial infarction
- Cerebral hemorrhage
- Cerebral thrombosis
- Hypertension
- Gallbladder disease
- Hepatic adenomas or benign liver tumors

There is evidence of an association between the following conditions and the use of oral contraceptives:

- Mesenteric thrombosis
- Retinal thrombosis

The following adverse reactions have been reported in patients receiving oral contraceptives and are believed to be drug related:

- Nausea
- Vomiting
- Gastrointestinal symptoms (such as abdominal cramps and bloating)
- Breakthrough bleeding
- Spotting
- Change in menstrual flow
- Amenorrhea
- Temporary infertility after discontinuation of treatment
- Edema/fluid retention
- Melasma/chloasma which may persist
- Breast changes: tenderness, enlargement, and secretion
- Change in weight or appetite (increase or decrease)
- Change in cervical ectropion and secretion
- Possible diminution in lactation when given immediately postpartum
- Cholestatic jaundice
- Migraine headache
- Rash (allergic)
- Mood changes, including depression
- Vaginitis, including candidiasis
- Change in corneal curvature (steepening)
- Intolerance to contact lenses
- Decrease in serum folate levels
- Exacerbation of systemic lupus erythematosus
- Exacerbation of porphyria
- Exacerbation of chorea
- Aggravation of varicose veins
- Anaphylactic/anaphylactoid reactions, including urticaria, angioedema, and severe reactions with respiratory and circulatory symptoms

The following adverse reactions have been reported in users of oral contraceptives and the association has been neither confirmed nor refuted:

- Premenstrual syndrome
- Cataracts
- Optic neuritis which may lead to partial or complete loss of vision
- Cystitis-like syndrome
- Headache
- Nervousness
- Dizziness
- Hirsutism
- Loss of scalp hair
- Erythema multiforme
- Erythema nodosum
- Hemorrhagic eruption
- Impaired renal function
- Hemolytic uremic syndrome
- Budd-Chiari syndrome
- Acne
- Changes in libido
- Colitis
- Pancreatitis
- Dysmenorrhea

OVERDOSAGE

Serious ill effects have not been reported following acute ingestion of large doses of oral contraceptives by young children.

Overdosage may cause nausea, and withdrawal bleeding may occur in females.

NONCONTRACEPTIVE HEALTH BENEFITS

The following noncontraceptive health benefits related to the use of oral contraceptives are supported by epidemiological studies which largely utilized oral contraceptive formulations containing doses exceeding 0.035 mg of ethinyl estradiol or 0.05 mg of mestranol.

Effects on menses:

- May decrease blood loss and may decrease incidence of iron-deficiency anemia
- May decrease incidence of dysmenorrhea

Effects related to inhibition of ovulation:

- May decrease incidence of functional ovarian cysts
- May decrease incidence of ectopic pregnancies

Effects from long-term use:

- May decrease incidence of fibroadenomas and fibrocystic disease of the breast
- May decrease incidence of acute pelvic inflammatory disease
- May decrease incidence of endometrial cancer
- May decrease incidence of ovarian cancer

DOSAGE AND ADMINISTRATION

Although the occurrence of pregnancy is unlikely if Jolessa™ is taken according to directions, if withdrawal bleeding does not occur while taking white (inactive) tablets, the possibility of pregnancy must be considered. Appropriate diagnostic measures to rule out pregnancy should be taken at the time of any missed menstrual period. Jolessa™ should be discontinued if pregnancy is confirmed.

The dosage of Jolessa™ is one pink (active) tablet daily for 84 consecutive days, followed by 7 days of white (inert) tablets. To achieve maximum contraceptive effectiveness, Jolessa™ must be taken exactly as directed and at intervals not exceeding 24 hours. Ideally, the tablets should be taken at the same time of the day on each day of active treatment. The tablets should not be removed from the protective blister packaging to avoid damage to the product. The dispenser card should be kept in the foil pouch until dispensed to the patient.

During the first cycle of medication, the patient is instructed to begin taking Jolessa™ on the first Sunday after the onset of menstruation. If menstruation begins on a Sunday, the first tablet (pink) is taken that day. One pink tablet should be taken daily for 84 consecutive days, followed by 7 days on which a white (inert) tablet is taken. Withdrawal bleeding should occur during the 7 days following discontinuation of pink active tablets. During the first cycle, contraceptive reliance should not be placed on Jolessa™ until a pink (active) tablet has been taken daily for 7 consecutive days and a non-hormonal back-up method of birth control (such as condoms or spermicide) should be used during those 7 days. The possibility of ovulation and conception prior to initiation of medication should be considered.

The patient begins her next and all subsequent 91-day courses of tablets without interruption on the same day of the week (Sunday) on which she began her first course, following the same schedule: 84 days on which pink tablets are taken followed by 7 days on which white tablets are taken. If in any cycle the patient starts tablets later than the proper day, she should protect herself against pregnancy by using a non-hormonal back-up method of birth control until she has taken a pink tablet daily for 7 consecutive days.

If spotting or breakthrough bleeding occurs, the patient is instructed to continue on the same regimen. This type of bleeding may be transient and without significance; however, if the bleeding is persistent or prolonged, the patient is advised to consult her healthcare provider.

For patient instructions regarding missed pills, see the “WHAT TO DO IF YOU MISS PILLS” section in the DETAILED PATIENT LABELING. Any time the patient misses two or more pink tablets, she should also use another method of nonhormonal back-up contraception until she has taken a pink tablet daily for seven consecutive days. If the patient misses one or more white tablets, she is still protected against pregnancy provided she begins taking pink tablets again on the proper day. The possibility of ovulation increases with each successive day that scheduled pink tablets are missed. The risk of pregnancy increases with each active (pink) tablet missed.

In the nonlactating mother, Jolessa™ may be initiated no earlier than day 28 postpartum, for contraception due to the increased risk for thromboembolism. When the tablets are administered in the postpartum period, the increased risk of thromboembolic disease associated with the postpartum period must be considered (See CONTRAINDICATIONS, WARNINGS and PRECAUTIONS concerning thromboembolic disease). The patient should be advised to use a nonhormonal back-up method for the first 7 days of tablet-taking. However, if intercourse has already occurred, the possibility of ovulation and conception prior to initiation of medication should be considered. Jolessa™ may be initiated immediately after a first-trimester abortion; if the patient starts Jolessa™ immediately, additional contraceptive measures are not needed.

HOW SUPPLIED

Jolessa™ tablets (levonorgestrel / ethinyl estradiol tablets) 0.15 mg / 0.03 mg are available in Extended-Cycle Tablet Dispensers, each containing a 13-week supply of tablets: 84 pink tablets, each containing 0.15 mg of levonorgestrel and 0.03 mg ethinyl estradiol, and 7 white inert tablets. The active pink tablets are round, film-coated, unscored, debossed with stylized b on one side and 992 on the other side. The white inert tablets are round, unscored, debossed with stylized b on one side and 208 on the other side.

Available in dispenser of 91 tablets | NDC 54868-6044-0

Store at 20° to 25° C (68° to 77° F) [See USP Controlled Room Temperature].

References available upon request.

BRIEF SUMMARY PATIENT PACKAGE INSERT

This product (like all oral contraceptives) is intended to prevent pregnancy. It does not protect against HIV infection (AIDS) and other sexually transmitted diseases such as chlamydia, genital herpes, genital warts, gonorrhea, hepatitis B, and syphilis.

Oral contraceptives, also known as “birth control pills” or “the pill”, are taken to prevent pregnancy, and when taken correctly, have a failure rate of approximately 1.0% per year (1 pregnancy per 100 women per year of use). The typical failure rate of pill users is approximately 5% per year when women who miss pills are included.

For the majority of women, oral contraceptives can be taken safely. But for some women oral contraceptive use is associated with certain serious diseases that can be life threatening or may cause temporary or permanent disability or death. The risks associated with taking oral contraceptives increase significantly if you:

- smoke
- have high blood pressure, diabetes, high cholesterol or are obese
- have or have had clotting disorders, heart attack, stroke, angina pectoris, cancer of the breast or sex organs, jaundice, or malignant or benign liver tumors

You should not take the pill if you are pregnant.

Although cardiovascular disease risks may be increased with oral contraceptive use after age 40 in healthy, non-smoking women (even with the newer low-dose formulations), there are also greater potential health risks associated with pregnancy in older women.

Cigarette smoking increases the risk of serious cardiovascular side effects from oral contraceptive use. This risk increases with age and with the amount of smoking (15 or more cigarettes per day has been associated with a significantly increased risk) and is quite marked in women over 35 years of age. Women who use oral contraceptives should not smoke.

Most side effects of the pill are not serious. The most common are nausea, vomiting, bleeding or spotting between menstrual periods, weight gain, breast tenderness, and difficulty wearing contact lenses. Some of these side effects, especially nausea and vomiting, may subside within the first 3 months of use.

The serious side effects of the pill occur very infrequently, especially if you are in good health and do not smoke. However, you should know that the following medical conditions have been associated with or made worse by the pill:

1. Blood clots in the legs (thrombophlebitis), lungs (pulmonary embolism), stoppage or rupture of a blood vessel in the brain (stroke), blockage of blood vessels in the heart (heart attack or angina pectoris) or other organs of the body. As mentioned above, smoking increases the risk of heart attacks and strokes and subsequent serious medical consequences. Women with migraine also may be at increased risk of stroke when taking the pill.
2. Liver tumors, which may rupture and cause severe bleeding. A possible but not definite association has been found with the pill and liver cancer. However, liver cancers are extremely rare. The chance of developing liver cancer from using the pill is thus even rarer.
3. High blood pressure, although blood pressure usually returns to normal when the pill is stopped.

The symptoms associated with these serious side effects are discussed in the detailed patient information leaflet. Notify your healthcare provider if you notice any unusual physical disturbances while taking the pill. In addition, drugs such as rifampin, as well as some anticonvulsants and some antibiotics, and herbal preparations containing St. John’s Wort (hypericum perforatum) may decrease oral contraceptive effectiveness.

Breast cancer has been diagnosed slightly more often in women who use the pill than in women of the same age who do not use the pill. This very small increase in the number of breast cancer diagnoses gradually disappears during the 10 years after stopping use of the pill. It is not known whether the difference is caused by the pill. It maybe that women taking the pill were examined more often, so that breast cancer was more likely to be detected. You should have regular breast examinations by a healthcare provider and examine your own breasts monthly. Tell your healthcare provider if you have a family history of breast cancer or if you have had breast nodules or an abnormal mammogram. Women who currently have or have had breast cancer should not use hormonal contraceptives because breast cancer is usually a hormone-sensitive tumor.

Some studies have found an increase in the incidence of cancer or precancerous lesions of the cervix in women who use the pill. However, this finding may be related to factors other than the use of the pill.

Be sure to discuss any medical condition you may have with your healthcare provider. Your healthcare provider will take a medical and family history before prescribing oral contraceptives and will examine you. The physical examination may be delayed to another time if you request it and the healthcare provider believes that it is appropriate to postpone it. You should be reexamined at least once a year while taking oral contraceptives. The detailed patient information leaflet gives you further information which you should read and discuss with your healthcare provider.

What You Should Know About Your Menstrual Cycle When Taking Jolessa™

When you take Jolessa™, which has a 91-day treatment cycle, you should expect to have 4 menstrual periods per year (bleeding when you are taking the 7 white pills). However, you also should expect to have more bleeding or spotting between your menstrual periods than if you were taking an oral contraceptive with a 28-day treatment cycle. During the first Jolessa™ treatment cycle, about 1 in 3 women may have 20 or more days of unplanned bleeding or spotting (bleeding when you are taking pink pills). This bleeding or spotting tends to decrease during later cycles. Do not stop Jolessa™ because of the bleeding. If the spotting continues for more than 7 consecutive days or if the bleeding is heavy, call your healthcare provider.

If You Miss Your Menstrual Period When Taking Jolessa™

You should consider the possibility that you are pregnant if you miss your menstrual period (no bleeding on the days that you are taking white tablets). Since scheduled menstrual periods are less frequent when you are taking Jolessa™, notify your healthcare provider that you have missed your period and are taking Jolessa™. Also notify your healthcare provider if you have symptoms of pregnancy such as morning sickness or unusual breast tenderness. It is important that your healthcare provider evaluates you to determine if you are pregnant. Stop taking Jolessa™ if it is determined that you are pregnant.

HOW TO TAKE JOLESSA™

IMPORTANT POINTS TO REMEMBER BEFORE YOU START TAKING JOLESSA™

1. BE SURE TO READ THESE DIRECTIONS:
  • Before you start taking your pills.
  • Anytime you are not sure what to do.
2. THE RIGHT WAY TO TAKE JOLESSA™ IS TO TAKE ONE PILL EVERY DAY AT THE SAME TIME.
  If you miss pills you could get pregnant. This includes starting the pack late. The more pills you miss, the more likely you are to get pregnant.
3. MANY WOMEN MAY FEEL SICK TO THEIR STOMACH DURING THE FIRST FEW WEEKS OF TAKING PILLS.
  If you feel sick to your stomach, do not stop taking the pill. The problem will usually go away. If it doesn’t go away, check with your healthcare provider.
4. MANY WOMEN HAVE SPOTTING OR LIGHT BLEEDING DURING THE FIRST FEW MONTHS OF TAKING JOLESSA™. Do not stop taking your pills even if you are having irregular bleeding. If the bleeding lasts for more than 7 consecutive days, talk to your healthcare provider.
5. MISSING PILLS CAN ALSO CAUSE SPOTTING OR LIGHT BLEEDING, even when you make up these missed pills.
  On the days you take 2 pills to make up for missed pills, you could also feel a little sick to your stomach.
6. IF YOU HAVE VOMITING OR DIARRHEA, or IF YOU TAKE SOME MEDICINES, including some antibiotics and the herbal supplement St. John’s Wort, Jolessa™ may not work as well. Use a back-up method (such as condoms or spermicides) until you check with your healthcare provider.
7. IF YOU HAVE TROUBLE REMEMBERING TO TAKE JOLESSA™, talk to your healthcare provider about how to make pill-taking easier or about using another method of birth control.
8. IF YOU HAVE ANY QUESTIONS OR ARE UNSURE ABOUT THE INFORMATION IN THIS LEAFLET, call your healthcare provider.

BEFORE YOU START TAKING JOLESSA™

1. DECIDE WHAT TIME OF DAY YOU WANT TO TAKE YOUR PILL. It is important to take it at about the same time every day.
2. LOOK AT YOUR EXTENDED-CYCLE TABLET DISPENSER. Your Tablet Dispenser consists of 3 trays with cards that hold 91 individually sealed pills (a 13-week or 91-day cycle). The 91 pills consist of 84 pink pills (active pills with hormones) and 7 white pills, (inactive pills without hormone). Trays 1 and 2 each contain 28 pink pills (4 rows of 7 pills). Tray 3 contains 35 pills consisting of 28 pinks pills (4 rows of 7 pills) and 7 white pills (1 row of 7 pills).
3. ALSO FIND:
  • Where on the first row in the pack to start taking pills (upper left corner at the start arrow) and
  • In what order to take the pills (follow the weeks and arrow).
4. BE SURE YOU HAVE READY AT ALL TIMES ANOTHER KIND OF BIRTH CONTROL (such as condoms or spermicides), to use as a back-up in case you miss pills.

WHEN TO START JOLESSA™

1. Take the first “active” pink pill on the Sunday after your period starts, even if you are still bleeding. If your period begins on Sunday, start the first pink pill that same day.
2. Use another method of birth control (such as condom or spermicide) as a back-up method if you have sex anytime from the Sunday you start your first pink pill until the next Sunday (first 7 days).

HOW TO TAKE JOLESSA™

1. Take one pill at the same time every day until you have taken the last pill in the tablet dispenser.
  Do not skip pills even if you are spotting or bleeding or feel sick to your stomach (nausea).
  Do not skip pills even if you do not have sex very often.
2. WHEN YOU FINISH A TABLET DISPENSER.
  After taking the last white pill, start taking the first pink pill from a new Extended-Cycle Tablet Dispenser the very next day regardless of when your period started. This should be on a Sunday.
3. If you miss your period when you are taking the white pills, call your healthcare provider because you may be pregnant.

WHAT TO DO IF YOU MISS PILLS

If you MISS 1 pink “active” pill:

1. Take it as soon as you remember. Take the next pill at your regular time. This means you may take 2 pills in 1 day.
2. You do not need to use a back-up birth control method if you have sex.

If you MISS 2 pink “active” pills in a row:

1. Take 2 pills on the day you remember, and 2 pills the next day.
2. Then take 1 pill a day until you finish the pack.
3. You COULD BECOME PREGNANT if you have sex in the 7 days after you restart your pills. You MUST use another birth control method (such as condoms or spermicide) as a back-up on the 7 days after you restart your pills.

If you MISS 3 OR MORE pink “active” pills in a row:

1. Do not remove the missed pills from the pack as they will not be taken. Keep taking 1 pill every day as indicated on the pack until you have completed all of the remaining pills in the pack. For example: If you resume taking the pill on Thursday, take the pill under “Thursday” and do not take the missed pills. You may experience bleeding during the week following the missed pills.
2. You COULD BECOME PREGNANT if you have sex during the days of missed pills or during the first 7 days after restarting your pills.
3. You must use a non-hormonal birth control method (such as condoms or spermicide) as a back-up when you miss pills and for the first 7 days after you restart your pills. If you miss your period when taking the white pills, call your healthcare provider because you may be pregnant.

If you MISS ANY of the 7 white inactive pills.

1. Throw away the missed pills.
2. Keep taking the scheduled pills until the pack is finished.
3. You do not need a back-up method of birth control.

FINALLY, IF YOU ARE STILL NOT SURE WHAT TO DO ABOUT THE PILLS YOU HAVE MISSED

1. Use a BACK-UP METHOD anytime you have sex.
2. KEEP TAKING ONE PILL EACH DAY until you contact your healthcare provider.

DETAILED PATIENT LABELING

This product (like all oral contraceptives) is intended to prevent pregnancy. Oral contraceptives do not protect against transmission of HIV (AIDS) and other sexually transmitted diseases such as chlamydia, genital herpes, genital warts, gonorrhea, hepatitis B, and syphilis.

INTRODUCTION

Any woman who considers using oral contraceptives (“the birth control pill” or “the pill”) should understand the benefits and risks of using this form of birth control. Although oral contraceptives have important advantages over other methods of contraception, they have certain risks that no other method has, and some of these risks may continue after you have stopped using the oral contraceptive. This leaflet will give you much of the information you will need to make this decision and will also help you determine if you are at risk of developing any of the serious side effects of the pill. It will tell you how to use Jolessa™ properly so that it will be as effective as possible. However, this leaflet is not a replacement for a careful discussion between you and your healthcare provider. You should discuss the information provided in this leaflet with your healthcare provider, both when you first start taking Jolessa™ and during your revisits. You should also follow your healthcare provider's advice with regard to regular check-ups while you are on Jolessa™.

EFFECTIVENESS OF ORAL CONTRACEPTIVES

Oral contraceptives or “the birth control pill” or “the pill” are used to prevent pregnancy and are more effective than most other nonsurgical methods of birth control. The chance of becoming pregnant is approximately 1.0% per year (1 pregnancy per 100 women per year of use) when the pills are used correctly, and no pills are missed. Typical failure rates are approximately 5.0% per year when women who miss pills are included. The chance of becoming pregnant increases with each missed pill during the menstrual cycle.

In comparison, typical failure rates for other methods of birth control during the first year of use are as follows:

No methods: 85%

Vaginal sponge: 20 to 40%

Cervical cap: 20 to 40%

Spermicides alone: 26%

Periodic abstinence: 25%

Condom (female): 21%

Diaphragm with spermicides: 20%

Withdrawal: 19%

Condom (male): 14%

Female sterilization: 0.5%

IUD: 0.1 to 2.0%

Injectable progestogen: 0.3%

Male sterilization: 0.15%

Norplant system: 0.05%

WHO SHOULD NOT TAKE ORAL CONTRACEPTIVES

Cigarette smoking increases the risk of serious cardiovascular side effects from oral contraceptive use. This risk increases with age and with the amount of smoking (15 or more cigarettes per day has been associated with a significantly increased risk) and is quite marked in women over 35 years of age. Women who use oral contraceptives should not smoke.

Some women should not use the pill. You should not use the pill if you have any of the following conditions:

- A history of heart attack or stroke
- A history of blood clots in the legs (thrombophlebitis), lungs (pulmonary embolism), or eyes
- A history of blood clots in the deep veins of your legs
- Chest pain (angina pectoris)
- Known or suspected breast cancer or cancer of the lining of the uterus, cervix, vagina, or certain hormonally-sensitive cancers
- Unexplained vaginal bleeding (until a diagnosis is reached by your healthcare provider)
- Yellowing of the whites of the eyes or of the skin (jaundice) during pregnancy or during previous use of the pill
- Liver tumor (benign or cancerous)
- Known or suspected pregnancy
- Heart valve or heart rhythm disorders that may be associated with formation of blood clots
- Diabetes affecting your circulation
- Uncontrolled high blood pressure
- Active liver disease with abnormal liver function tests
- Allergy or hypersensitivity to any of the components of Jolessa™
- A need for surgery with prolonged bedrest

Tell your healthcare provider if you have any of the above conditions. Your healthcare provider can recommend a safer method of birth control.

OTHER CONSIDERATIONS BEFORE TAKING ORAL CONTRACEPTIVES

Tell your healthcare provider if you or any family member has ever had:

- Breast nodules, fibrocystic disease of the breast, an abnormal breast X-ray or mammogram
- Diabetes
- Elevated cholesterol or triglycerides
- High blood pressure
- Migraine or other headaches or epilepsy
- Depression
- Gallbladder, liver, heart or kidney disease
- History of scanty or irregular menstrual periods

Women with any of these conditions should be checked often by their healthcare provider if they choose to use oral contraceptives. Also, be sure to inform your healthcare provider if you smoke or are on any medications.

RISKS OF TAKING ORAL CONTRACEPTIVES

If you use Jolessa™ you will receive more exposure to hormones on a yearly basis than if you used a conventional 28-day cycle oral contraceptives containing a similar amount of estrogen and progestin (an additional 9 weeks exposure per year). While this added exposure may pose an additional risk of thrombotic and thromboembolic disease, studies to date with Jolessa™ have not suggested an increased risk of these disorders.

1. Risk of Developing Blood Clots

Blood clots and blockage of blood vessels are the most serious side effects of taking oral contraceptives and can cause death or serious disability. In particular, a clot in the legs can cause thrombophlebitis and a clot that travels to the lungs can cause a sudden blocking of the vessel carrying blood to the lungs. Rarely, clots occur in the blood vessels of the eye and may cause blindness, double vision, or impaired vision.

If you take oral contraceptives and need elective surgery, need to stay in bed for a prolonged illness, or have recently delivered a baby, you may be at risk of developing blood clots. You should consult your healthcare provider about stopping oral contraceptives three to four weeks before surgery and not taking oral contraceptives for two weeks after surgery or during bed rest. You should also not take oral contraceptives soon after delivery of a baby. It is advisable to wait for at least four weeks after delivery if you are not breastfeeding. If you are breastfeeding, you should wait until you have weaned your child before using the pill (See also the section on Breastfeeding in “GENERAL PRECAUTIONS.”)

The risk of circulatory disease in oral contraceptive users may be higher in users of high-dose pills (containing 50 micrograms or higher of ethinyl estradiol) and may be greater with longer duration of oral contraceptive use. In addition, some of these increased risks may continue for a number of years after stopping oral contraceptives. The risk of abnormal blood clotting increases with age in both users and nonusers of oral contraceptives, but the increased risk from the oral contraceptive appears to be present at all ages. For women aged 20 to 44, it is estimated that about 1 in 2,000 using oral contraceptives will be hospitalized each year because of abnormal clotting.

Among nonusers in the same age group, about 1 in 20,000 would be hospitalized each year. For oral contraceptive users in general, it has been estimated that in women between the ages of 15 and 34 the risk of death due to a circulatory disorder is about 1 in 12,000 per year, whereas for nonusers the rate is about 1 in 50,000 per year. In the age group 35 to 44, the risk is estimated to be about 1 in 2,500 per year for oral contraceptive users and about 1 in 10,000 per year for nonusers.

2. Heart Attacks and Strokes

Oral contraceptives may increase the tendency to develop strokes (stoppage or rupture of blood vessels in the brain) and angina pectoris and heart attacks (blockage of blood vessels in the heart). Any of these conditions can cause death or serious disability.

Smoking greatly increases the possibility of suffering heart attacks and strokes. Furthermore, smoking and the use of oral contraceptives greatly increase the chances of developing and dying of heart disease.

Women with migraine (especially migraine with aura) who take oral contraceptives also may be at higher risk of stroke.

3. Gallbladder Disease

Oral contraceptive users probably have a greater risk than nonusers of having gallbladder disease, although this risk may be related to pills containing high doses of estrogens.

4. Liver Tumors

In rare cases, oral contraceptives can cause benign but dangerous liver tumors. These benign liver tumors can rupture and cause fatal internal bleeding. In addition, a possible but not definite association has been found with the pill and liver cancers in two studies in which a few women who developed these very rare cancers were found to have used oral contraceptives for long periods. However, liver cancers in general are extremely rare and the chance of developing liver cancer from using the pill is thus even rarer.

5. Cancer of the Breast and Reproductive Organs

Breast cancer has been diagnosed slightly more often in women who use the pill than in women of the same age who do not use the pill. This small increase in the number of breast cancer diagnoses gradually disappears during the 10 years after stopping use of the pill. It is not known whether the difference is caused by the pill. It may be that women taking the pill are examined more often, so that breast cancer is more likely to be detected. You should have regular breast examinations by a healthcare provider and examine your own breasts monthly. Tell your healthcare provider if you have a family history of breast cancer or if you have had breast nodules or an abnormal mammogram.

Women who currently have or have had breast cancer should not use oral contraceptives because breast cancer is usually a hormone-sensitive tumor.

Some studies have found an increase in the incidence of cancer or precancerous lesions of the cervix in women who use oral contraceptives. However, this finding may be related to factors other than the use of oral contraceptives. There is insufficient evidence to rule out the possibility that the pill may cause such cancers.

6. Lipid Metabolism and Inflammation of the Pancreas

In patients with inherited defects of the lipid metabolism, there have been reports of significant elevations of plasma triglycerides during estrogen therapy. This has led to pancreatitis in some cases.

ESTIMATED RISK OF DEATH FROM A BIRTH CONTROL METHOD OR PREGNANCY

All methods of birth control and pregnancy are associated with a risk of developing certain diseases which may lead to disability or death. An estimate of the number of deaths associated with different methods of birth control and pregnancy has been calculated and is shown in the following table.

ANNUAL NUMBER OF BIRTH-RELATED OR METHOD-RELATED DEATHS ASSOCIATED WITH CONTROL OF FERTILITY PER 100,000 NONSTERILE WOMEN, BY FERTILITY-CONTROL METHOD AND ACCORDING TO AGE
AGE
Method of control and outcome | 15-19 | 20-24 | 25-29 | 30-34 | 35-39 | 40-44
No fertility - control methods* | 7.0 | 7.4 | 9.1 | 14.8 | 25.7 | 28.2
Oral contraceptives non-smoker† | 0.3 | 0.5 | 0.9 | 1.9 | 13.8 | 31.6
Oral contraceptives smoker† | 2.2 | 3.4 | 6.6 | 13.5 | 51.1 | 117.2
IUD† | 0.8 | 0.8 | 1.0 | 1.0 | 1.4 | 1.4
Condom* | 1.1 | 1.6 | 0.7 | 0.2 | 0.3 | 0.4
Diaphragm/ spermicide* | 1.9 | 1.2 | 1.2 | 1.3 | 2.2 | 2.8
Periodic abstinence* | 2.5 | 1.6 | 1.6 | 1.7 | 2.9 | 3.6

*Deaths are birth related†Deaths are method related

In the above table, the risk of death from any birth control method is less than the risk of childbirth, except for oral contraceptive users over the age of 35 who smoke and pill users over the age of 40 even if they do not smoke. It can be seen in the table that for women aged 15 to 39, the risk of death was highest with pregnancy (7 to 26 deaths per 100,000 women, depending on age). Among pill users who do not smoke, the risk of death was always lower than that associated with pregnancy for any age group, although over the age of 40, the risk increases to 32 deaths per 100,000 women, compared to 28 associated with pregnancy at that age. However, for pill users who smoke and are over the age of 35, the estimated number of deaths exceeds those for other methods of birth control. If a woman is over the age of 40 and smokes, her estimated risk of death is four times higher (117/100,000 women) than the estimated risk associated with pregnancy (28/100,000 women) in that age group.

The suggestion that women over 40 who don't smoke should not take oral contraceptives is based on information from older high-dose pills. An Advisory Committee of the FDA discussed this issue in 1989 and recommended that the benefits of oral contraceptive use by healthy, nonsmoking women over 40 years of age may outweigh the possible risks. Older women, as all women who take oral contraceptives, should take an oral contraceptive that contains the least amount of estrogen and progestin that is compatible with the individual patient needs.

WARNING SIGNALS

If any of these adverse effects occur while you are taking oral contraceptives, call your healthcare provider immediately:

- Sharp chest pain, coughing of blood, or sudden shortness of breath (indicating a possible clot in the lung).
- Pain in the calf (indicating a possible clot in the leg).
- Crushing chest pain or heaviness in the chest (indicating a possible heart attack).
- Sudden severe headache or vomiting, dizziness or fainting, disturbances of vision or speech, weakness, or numbness in an arm or leg (indicating a possible stroke).
- Sudden partial or complete loss of vision (indicating a possible clot in the eye).
- Breast lumps (indicating possible breast cancer or fibrocystic disease of the breast; ask your doctor or healthcare provider to show you how to examine your breasts).
- Severe pain or tenderness in the stomach area (indicating a possibly ruptured liver tumor).
- Difficulty in sleeping, weakness, lack of energy, fatigue, or change in mood (possibly indicating severe depression).
- Jaundice or a yellowing of the skin or eyeballs, accompanied frequently by fever, fatigue, loss of appetite, dark-colored urine, or light-colored bowel movements (indicating possible liver problems).

SIDE EFFECTS OF ORAL CONTRACEPTIVES

In addition to the risks and more serious side effects discussed above (see RISKS OF TAKING ORAL CONTRACEPTIVES, ESTIMATED RISK OF DEATH FROM A BIRTH CONTROL METHOD OR PREGNANCY and WARNING SIGNALS sections), the following may also occur:

1. Irregular vaginal bleeding

Irregular vaginal bleeding or spotting (bleeding or spotting between your expected period) is likely to occur while you are taking Jolessa™. Irregular bleeding may vary from slight staining between menstrual periods to breakthrough bleeding which is a flow much like a regular period. Irregular bleeding occurs most often during the first few 91-day cycles of Jolessa™ use, tends to decrease during later cycles, but may also occur after you have been taking Jolessa™ for some time. Such bleeding usually does not indicate any serious problems. It is important to continue taking your pills on schedule even if you are having irregular bleeding. If the bleeding lasts for more than 7 consecutive days, talk to your healthcare provider.

When you take Jolessa™, you need to consider the convenience of fewer expected menstrual periods (4 per year instead of 13) and the inconvenience of more irregular vaginal bleeding or spotting. In a clinical trial comparing Jolessa™ (91-day cycles) to a conventional equivalent dosage 28-day cycle oral contraceptive, more women using Jolessa™ discontinued treatment because of bleeding problems (7.7% of the Jolessa™ users compared to 1.8% of the 28-day cycle users).

The following Table shows the percentages of women with 7 or more and 20 or more days of intermenstrual bleeding and/or spotting in the Jolessa™ and the 28-day cycle treatment groups.

Percentages (%) of Women with Intermenstrual Bleeding and/or Spotting
Number of days of intermenstrual bleeding and/or spotting | Percentage of subjects with intermenstrual bleeding or spotting*
Jolessa™ | Cycle 1 | Cycle 4
7 or more days | 65% | 42%
20 or more days | 35% | 15%
28-day cycle pill | Cycles 1-4 | Cycles 10-13
7 or more | 38% | 39%
20 or more days | 6% | 4%

*Based on spotting and/or bleeding on days 1-84 of a 91 day cycle in the Jolessa™ subjects and days 1-21 of a 28 day cycle over 4 cycles in the 28-day dosing regimen.

Total days of bleeding and/or spotting (withdrawal plus intermenstrual) were similar over one year of treatment for Jolessa™ subjects and subjects on the 28-day cycle regimen.

2. Contact lenses

If you wear contact lenses and notice a change in vision or an inability to wear your lenses, contact your healthcare provider.

3. Fluid retention

Oral contraceptives may cause edema (fluid retention) with swelling of the fingers or ankles and may raise your blood pressure. If you experience fluid retention, contact your healthcare provider.

4. Melasma

A spotty darkening of the skin is possible, particularly of the face.

5. Other side effects

Other side effects may include nausea and vomiting, change in appetite, breast tenderness, headache, nervousness, depression, dizziness, loss of scalp hair, rash, vaginal infections, and allergic reactions.

If any of these side effects bother you, call your healthcare provider.

GENERAL PRECAUTIONS

1. Missed Periods and Use of Oral Contraceptives Before or During Early Pregnancy

If you miss any periods (no bleeding on the days that you take white pills), you must consider the possibility that you may be pregnant. Notify your healthcare provider that you are taking Jolessa™ and have missed your period. Also notify your healthcare provider if you have any symptoms of pregnancy such as morning sickness or unusual breast tenderness. Because you are taking Jolessa™, it is very important that your healthcare provider evaluates you to determine if you are pregnant. Stop taking Jolessa™ if you are pregnant.

There is no conclusive evidence that oral contraceptive use is associated with an increase in birth defects, when taken inadvertently during early pregnancy. Previously, a few studies had reported that oral contraceptives might be associated with birth defects, but these studies have not been confirmed. Nevertheless, oral contraceptives should not be used during pregnancy. You should check with your healthcare provider about risks to your unborn child of any medication taken during pregnancy.

2. While Breastfeeding

If you are breastfeeding, consult your healthcare provider before starting oral contraceptives. Some of the drug will be passed on to the child in the milk. A few adverse effects on the child have been reported, including yellowing of the skin (jaundice) and breast enlargement. In addition, oral contraceptives may decrease the amount and quality of your milk. If possible, do not use oral contraceptives while breastfeeding. You should use another method of contraception since breastfeeding provides only partial protection from becoming pregnant and this partial protection decreases significantly as you breast-feed for longer periods of time. You should consider starting oral contraceptives only after you have weaned your child completely.

3. Laboratory Tests

If you are scheduled for any laboratory tests, tell your healthcare provider you are taking birth control pills. Certain blood tests may be affected by birth control pills.

4. Drug Interactions

Certain drugs may interact with birth control pills to make them less effective in preventing pregnancy or cause an increase in breakthrough bleeding. Such drugs include rifampin, drugs used for epilepsy such as barbiturates (for example, phenobarbital), carbamazepine (Tegretol is one brand of this drug), and phenytoin (Dilantin® is one brand of this drug), primidone (Mysoline®), topiramate (Topamax®), phenylbutazone (Butazolidin® is one brand), some drugs used for HIV such as ritonavir (Norvir®), modafinil (Provigil®) and possibly certain antibiotics (such as ampicillin and other penicillins, and tetracyclines). Pregnancies and breakthrough bleeding have been reported by users of combined hormonal contraceptives who also used some form of the herbal supplement St. John’s Wort. You may need to use a non-hormonal method of contraception during any cycle in which you take drugs that can make oral contraceptives less effective. Be sure to tell your healthcare provider if you are taking or start taking any other medications, including nonprescription products or herbal products while taking birth control pills.

You may be at higher risk of a specific type of liver dysfunction if you take troleandomycin and oral contraceptives at the same time.

Birth control pills may interact with lamotrigine, an anticonvulsant used for epilepsy. This may increase the risk of seizures, so your physician may need to adjust the dose of lamotrigine.

5. Sexually transmitted diseases

This product (like all oral contraceptives) is intended to prevent pregnancy. It does not protect against transmission of HIV (AIDS) and other sexually transmitted diseases such as chlamydia, genital herpes, genital warts, gonorrhea, hepatitis B, and syphilis.

What You Should Know About Your Menstrual Cycle When Taking Jolessa™

When you take Jolessa™, which has a 91-day treatment cycle, you should expect to have 4 menstrual periods per year (bleeding when you are taking the 7 white pills). However, you also should expect to have more bleeding or spotting between your menstrual periods than if you were taking an oral contraceptive with a 28-day treatment cycle. During the first Jolessa™ treatment cycle, about 1 in 3 women may have 20 or more days of unplanned bleeding or spotting (bleeding when you are taking pink pills). This bleeding or spotting tends to decrease during later cycles. Do not stop Jolessa™ because of the bleeding. If the spotting continues for more than 7 consecutive days or if the bleeding is heavy, call your healthcare provider.

HOW TO TAKE JOLESSA™

IMPORTANT POINTS TO REMEMBER BEFORE YOU START TAKING JOLESSA™

1. BE SURE TO READ THESE DIRECTIONS:
  • Before you start taking your pills.
  • Anytime you are not sure what to do.
2. THE RIGHT WAY TO TAKE JOLESSA™ IS TO TAKE ONE PILL EVERY DAY AT THE SAME TIME.
  If you miss pills you could get pregnant. This includes starting the pack late. The more pills you miss, the more likely you are to get pregnant.
3. MANY WOMEN MAY FEEL SICK TO THEIR STOMACH DURING THE FIRST FEW WEEKS OF TAKING PILLS.
  If you feel sick to your stomach, do not stop taking the pill. The problem will usually go away. If it doesn't go away, check with your healthcare provider.
4. MANY WOMEN HAVE SPOTTING OR LIGHT BLEEDING DURING THE FIRST FEW MONTHS OF TAKING JOLESSA™. Do not stop taking your pills even if you are having irregular bleeding. If the bleeding lasts for more than a few days, talk to your healthcare provider.
5. MISSING PILLS CAN ALSO CAUSE SPOTTING OR LIGHT BLEEDING, even when you make up these missed pills.
  On the days you take 2 pills to make up for missed pills, you could also feel a little sick to your stomach.
6. IF YOU HAVE VOMITING OR DIARRHEA, or IF YOU TAKE SOME MEDICINES, including some antibiotics and the herbal supplement St. John’s Wort, Jolessa™ may not work as well. Use a back-up method (such as condoms or spermicides) until you check with your healthcare provider.
7. IF YOU HAVE TROUBLE REMEMBERING TO TAKE JOLESSA™, talk to your healthcare provider about how to make pill-taking easier or about using another method of birth control.
8. IF YOU HAVE ANY QUESTIONS OR ARE UNSURE ABOUT THE INFORMATION IN THIS LEAFLET, call your healthcare provider.

BEFORE YOU START TAKING JOLESSA™

1. DECIDE WHAT TIME OF DAY YOU WANT TO TAKE YOUR PILL. It is important to take it at about the same time every day.
2. LOOK AT YOUR EXTENDED-CYCLE TABLET DISPENSER. Your Tablet Dispenser consists of 3 trays with cards that hold 91 individually sealed pills (a 13-week or 91-day cycle). The 91 pills consist of 84 pink pills (active pills with hormones) and 7 white pills, (inactive pills without hormone). Trays 1 and 2 each contain 28 pink pills (4 rows of 7 pills). Tray 3 contains 35 pills consisting of 28 pinks pills (4 rows of 7 pills) and 7 white pills (1 row of 7 pills).
3. ALSO FIND:
  • Where on the first row in the pack to start taking pills (upper left corner at the start arrow) and
  • In what order to take the pills (follow the weeks and arrow).
4. BE SURE YOU HAVE READY AT ALL TIMES ANOTHER KIND OF BIRTH CONTROL (such as condoms or spermicides), to use as a back-up in case you miss pills.

WHEN TO START JOLESSA™

1. Take the first “active” pink pill on the Sunday after your period starts, even if you are still bleeding. If your period begins on Sunday, start the first pink pill that same day.
2. Use another method of birth control (such as condom or spermicide) as a back-up method if you have sex anytime from the Sunday you start your first pink pill until the next Sunday (first 7 days).

HOW TO TAKE JOLESSA™

1. Take one pill at the same time every day until you have taken the last pill in the tablet dispenser.
  Do not skip pills even if you are spotting or bleeding or feel sick to your stomach (nausea).
  Do not skip pills even if you do not have sex very often.
2. WHEN YOU FINISH A TABLET DISPENSER.
  After taking the last white pill, start taking the first pink pill from a new Extended-Cycle Tablet Dispenser the very next day regardless of when your period started. This should be on a Sunday.
3. If you miss your period when you are taking the white pills, call your healthcare provider because you may be pregnant.

WHAT TO DO IF YOU MISS PILLS

If you MISS 1 pink “active” pill:

1. Take it as soon as you remember. Take the next pill at your regular time. This means you may take 2 pills in 1 day.
2. You do not need to use a back-up birth control method if you have sex.

If you MISS 2 pink “active” pills in a row:

1. Take 2 pills on the day you remember, and 2 pills the next day.
2. Then take 1 pill a day until you finish the pack.
3. You COULD BECOME PREGNANT if you have sex in the 7 days after you restart your pills. You MUST use another birth control method (such as condoms or spermicide) as a back-up on the 7 days after you restart your pills.

If you MISS 3 OR MORE pink “active” pills in a row:

1. Do not remove the missed pills from the pack as they will not be taken. Keep taking 1 pill every day as indicated on the pack until you have completed all of the remaining pills in the pack. For example: If you resume taking the pill on Thursday, take the pill under “Thursday” and do not take the missed pills. You may experience bleeding during the week following the missed pills.
2. You COULD BECOME PREGNANT if you have sex during the days of missed pills or during the first 7 days after restarting your pills.
3. You must use a non-hormonal birth control method (such as condoms or spermicide) as a back-up when you miss pills and for the first 7 days after you restart your pills. If you miss your period when taking the white pills, call your healthcare provider because you may be pregnant.

If you MISS ANY of the 7 white inactive pills.

1. Throw away the missed pills.
2. Keep taking the scheduled pills until the pack is finished.
3. You do not need a back-up method of birth control.

FINALLY, IF YOU ARE STILL NOT SURE WHAT TO DO ABOUT THE PILLS YOU HAVE MISSED

1. Use a BACK-UP METHOD anytime you have sex.
2. KEEP TAKING ONE PILL EACH DAY until you contact your healthcare provider.

PREGNANCY DUE TO PILL FAILURE

If taken every day as directed, the incidence of pill failure resulting in pregnancy is approximately 1% (ie, one pregnancy per 100 women per year), but more typical failure rates are about 5%. If failure does occur, the risk to the fetus is minimal.

PREGNANCY AFTER STOPPING THE PILL

There may be some delay in becoming pregnant after you stop using oral contraceptives, especially if you had irregular menstrual cycles before you used oral contraceptives. It may be advisable to postpone conception until you begin menstruating regularly once you have stopped taking the pill and desire pregnancy.

There does not appear to be any increase in birth defects in newborn babies when pregnancy occurs soon after stopping the pill.

OVERDOSAGE

Serious ill effects have not been reported following ingestion of large doses of oral contraceptives by young children. Overdosage may cause nausea and withdrawal bleeding in females. In case of overdosage, contact your healthcare provider or pharmacist.

OTHER INFORMATION

Your healthcare provider will take a medical and family history before prescribing oral contraceptives and will examine you. The physical examination may be delayed to another time if you request it and the healthcare provider believes that it is appropriate to postpone it. You should be reexamined at least once a year. Be sure to inform your healthcare provider if there is a family history of any of the conditions listed previously in this leaflet. Be sure to keep all appointments with your healthcare provider, because this is a time to determine if there are early signs of side effects of oral contraceptive use.

Do not use the drug for any condition other than the one for which it was prescribed. This drug has been prescribed specifically for you; do not give it to others who may want birth control pills.

NONCONTRACEPTIVE HEALTH BENEFITS

The following noncontraceptive health benefits related to the use of oral contraceptives are supported by epidemiological studies which largely utilized oral contraceptive formulations containing doses exceeding 0.035 mg of ethinyl estradiol or 0.05 mg of mestranol.

Effects on menses:

- May decrease blood loss and may decrease incidence of iron-deficiency anemia
- May decrease incidence of dysmenorrhea

Effects related to inhibition of ovulation:

- May decrease incidence of functional ovarian cysts
- May decrease incidence of ectopic pregnancies

Effects from long-term use:

- May decrease incidence of fibroadenomas and fibrocystic disease of the breast
- May decrease incidence of acute pelvic inflammatory disease
- May decrease incidence of endometrial cancer
- May decrease incidence of ovarian cancer

If you want more information about birth control pills, ask your doctor or pharmacist. They have a more technical leaflet called the Professional Labeling which you may wish to read.

BARR LABORATORIES, INC.

Pomona, NY 10970

Revised February 2010

11001623

Relabeling of Additional barcode label by:

Physicians Total Care, Inc.
Tulsa, OK 74146

PRINCIPAL DISPLAY PANEL

1 Extended-Cycle Tablet Dispensers

91 Tablets Each 91 DAY REGIMEN

NDC 54868-6044-0

JolessaTM
(levonorgestrel / ethinyl estradiol tablets) 0.15 mg/0.03 mg

Contains 1 Extended-Cycle Tablet Dispensers, each containing 91 tablets: 84
pink tablets, each containing 0.15 mg levonorgestrel with 0.03 mg ethinyl
estradiol, and 7 white inert tablets.

Rx only

Store at 20° to 25°C (68° to 77°F)
[See USP Controlled Room Temperature].

Usual Dosage: One tablet daily for 91 consecutive days in the following order: 84 pink tablets followed by 7 white tablets as prescribed.

See enclosed package brochure.

Pharmacist: Dispense patient information with each prescription.

THIS PRODUCT (LIKE ALL ORAL CONTRACEPTIVES) IS INTENDED TO PREVENT PREGNANCY. IT DOES NOT PROTECT AGAINST HIV INFECTION (AIDS) AND OTHER SEXUALLY TRANSMITTED DISEASES.